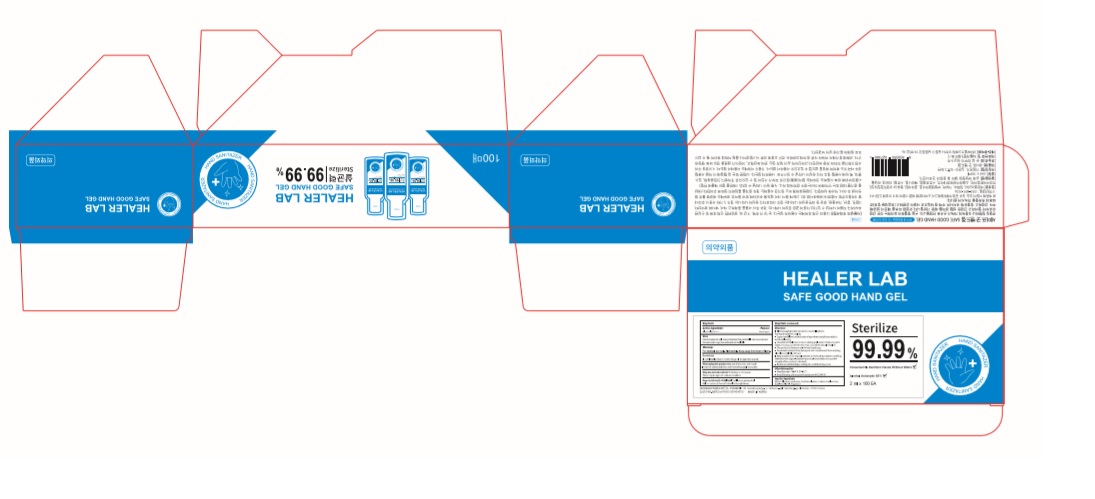 DRUG LABEL: HEALER LAB Safe good hand gel
NDC: 74339-0262 | Form: GEL
Manufacturer: PL COSMETIC
Category: otc | Type: HUMAN OTC DRUG LABEL
Date: 20200427

ACTIVE INGREDIENTS: ALCOHOL 1.24 mL/2 mL
INACTIVE INGREDIENTS: GLYCERIN; CARBOMER HOMOPOLYMER, UNSPECIFIED TYPE; WATER; BUTYLENE GLYCOL; HYALURONATE SODIUM; TROLAMINE

[HEALER LAB SAFE GOOD HAND Gel] 2 ml pouch x 100 EA : 74339-0262-2